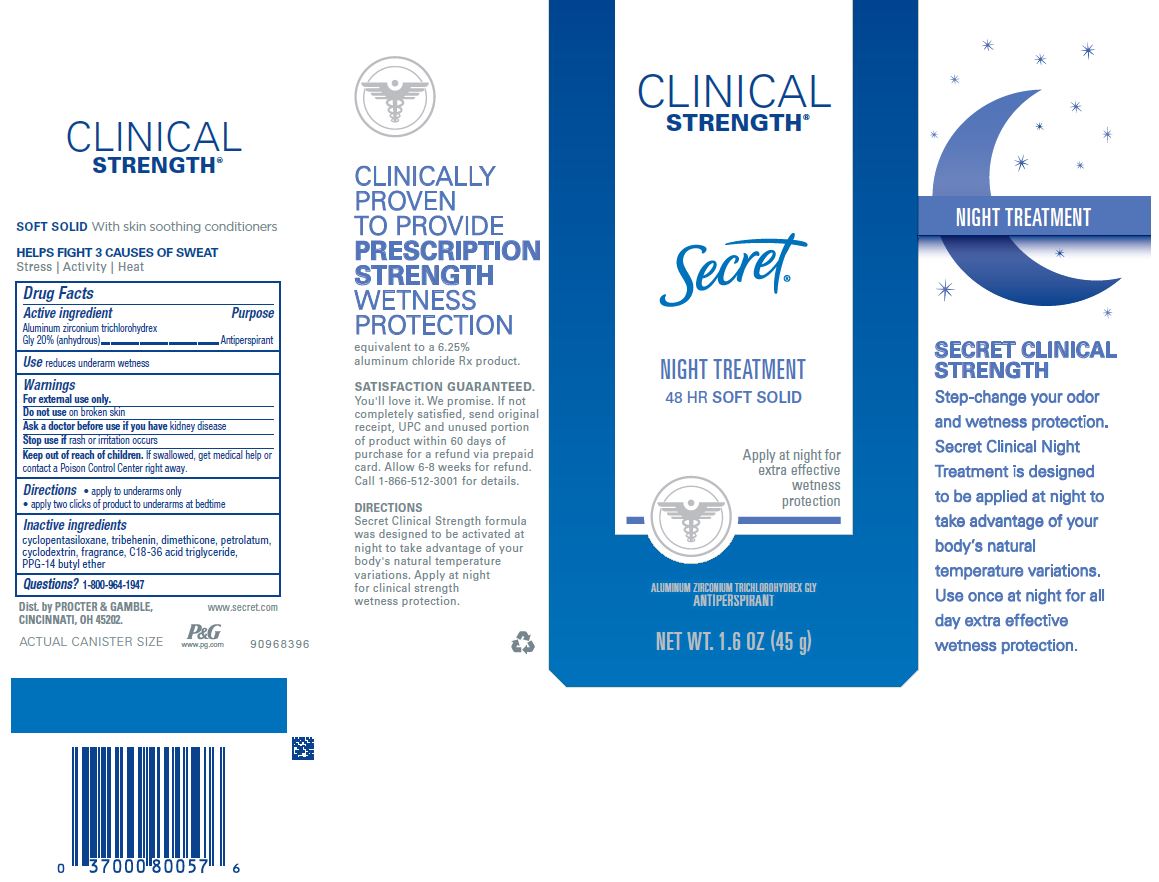 DRUG LABEL: Secret Clinical Strength Night Treatment Soft Soothing Lavender
NDC: 69423-331 | Form: CREAM
Manufacturer: The Procter & Gamble Manufacturing Company
Category: otc | Type: HUMAN OTC DRUG LABEL
Date: 20200205

ACTIVE INGREDIENTS: ALUMINUM ZIRCONIUM TRICHLOROHYDREX GLY 20 g/100 g
INACTIVE INGREDIENTS: BETADEX; C18-36 ACID TRIGLYCERIDE; CYCLOMETHICONE 5; DIMETHICONE; PETROLATUM; TRIBEHENIN; PPG-14 BUTYL ETHER

Secret® Clinical Strength Night Treatment Soft Solid Soothing Lavender

Drug Facts

Active ingredient

Aluminum zirconium trichlorohydrex Gly 20% (anhydrous)

Purpose

Antiperspirant

Use

- reduces underarm wetness

Warnings

For external use only.

Do not use on broken skin

Ask a doctor before use if you have kidney disease

Stop use if rash or irritation occurs

Keep out of reach of children. If swallowed, get medical help or contact a Poison Control Center right away.

Directions

- apply to underarms only
- apply two clicks of product to underarms at bedtime

Inactive ingredients

cyclopentasiloxane, tribehenin, dimethicone, petrolatum, cyclodextrin, fragrance, C18-36 acid triglyceride, PPG-14 butyl ether

Questions?

1-800-964-1947

Dist. by PROCTER & GAMBLE,
CINCINNATI, OH 45202.

PRINCIPAL DISPLAY PANEL - 45 g Cylinder Carton

Secret®

CLINICAL
STRENGTH®

NIGHT

TREATMENT

48 HR Soft Solid

ALUMINUM ZIRCONIUM TRICHLOROHYDREX GLY
ANTIPERSPIRANT/DEODORANT

NET WT. 1.6 OZ. (45 g)